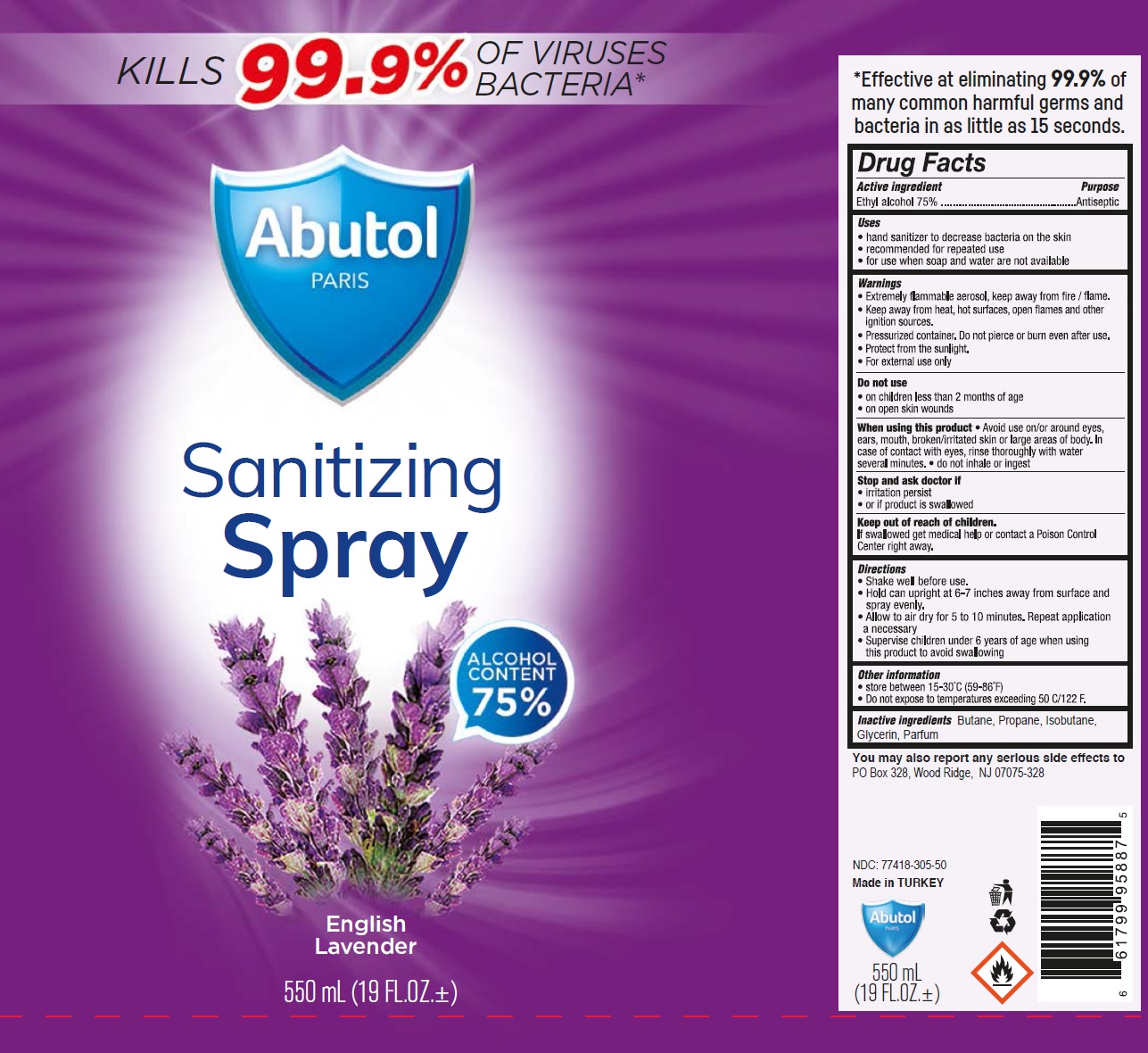 DRUG LABEL: Abutol Sanitizing English Lavender
NDC: 77418-305 | Form: SPRAY
Manufacturer: ATAK FARMA KOZMETIK VE KIMYA SANAYI TICARET ANONIM SIRKETI
Category: otc | Type: HUMAN OTC DRUG LABEL
Date: 20201028

ACTIVE INGREDIENTS: ALCOHOL 75 mL/100 mL
INACTIVE INGREDIENTS: BUTANE; PROPANE; ISOBUTANE; GLYCERIN

Abutol PARIS Sanitizing Spray English Lavender

Active ingredient

Ethyl alcohol 75%

Purpose

Antiseptic

Uses

• hand sanitizer to decrease bacteria on the skin
• recommended for repeated use
• for use when soap and water are not available

Warnings

• Extremely flammable aerosol, keep away from fire / flame.

• Keep away from heat, hot surfaces, open flames and other ignition sources.

• Pressurized container. Do not pierce or burn even after use.

• Protect from the sunlight.

• For external use only

Do not use

• on children less than 2 months of age

• on open skin wounds

When using this product • Avoid use on/or around eyes, ears, mouth, broken/irritated skin or large areas of body. In case of contact with eyes, rinse thoroughly with water several minutes. • do not inhale or ingest

Stop and ask doctor if

• irritation persist

• or if product is swallowed

Keep out of reach of children.

If swallowed get medical help or contact a Poison Control Center right away.

Directions

• Shake well before use.

• Hold can upright at 6-7 inches away from surface and spray evenly.

• Allow to air dry for 5 to 10 minutes. Repeat application a necessary

• Supervise children under 6 years of age when using this product to avoid swallowing

Other information

• store between 15-30°C (59-86°F)
• Do not expose to temperatures exceeding 50 C/122 F.

Inactive ingredients

Butane, Propane, Isobutane, Glycerin, Parfum

KILLS 99.9% OF VIRUSES BACTERIA*

ALCOHOL CONTENT 75%

*Effective at eliminating 99.9% of many common harmful germs and bacteria in as little as 15 seconds.

You may also report any serious side effects to PO Box 328, Wood Ridge, NJ 07075-328

Made in TURKEY